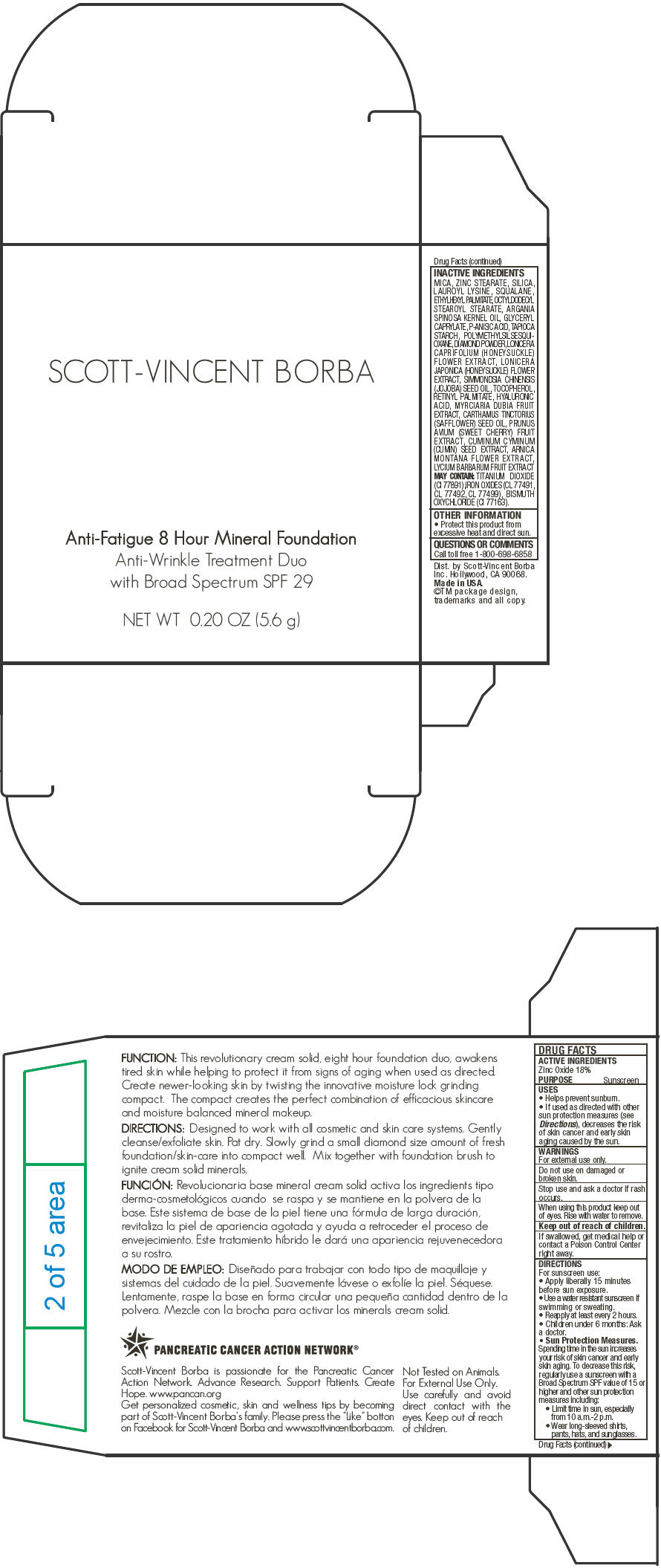 DRUG LABEL: Scott-Vincent Borba 
NDC: 51625-001 | Form: POWDER
Manufacturer: Scott-Vincent Borba
Category: otc | Type: HUMAN OTC DRUG LABEL
Date: 20120620

ACTIVE INGREDIENTS: Zinc Oxide 18 g/100 g
INACTIVE INGREDIENTS: MICA; ZINC STEARATE; SILICON DIOXIDE; LAUROYL LYSINE; SQUALANE; ETHYLHEXYL PALMITATE; OCTYLDODECYL STEAROYL STEARATE; ARGAN OIL; GLYCERYL CAPRYLATE; P-ANISIC ACID; STARCH, TAPIOCA; DIAMOND; LONICERA CAPRIFOLIUM FLOWER; LONICERA JAPONICA FLOWER; JOJOBA OIL; TOCOPHEROL; VITAMIN A PALMITATE; HYALURONIC ACID; MYRCIARIA DUBIA FRUIT; SAFFLOWER OIL; SWEET CHERRY; CUMIN; ARNICA MONTANA FLOWER; LYCIUM BARBARUM FRUIT; TITANIUM DIOXIDE; BISMUTH OXYCHLORIDE

Scott-Vincent Borba
Anti-Fatigue 8 Hour Mineral Foundation with Broad Spectrum SPF 29

DRUG FACTS

ACTIVE INGREDIENTS

Zinc Oxide 18%

PURPOSE

Sunscreen

USES

- Helps prevent sunburn.
- If used as directed with other sun protection measures (see Directions), decreases the risk of skin cancer and early skin aging caused by the sun.

WARNINGS

For external use only.

Do not use on damaged or broken skin.

Stop use and ask a doctor if rash occurs.

When using this product keep out of eyes. Rise with water to remove.

Keep out of reach of children.

If swallowed, get medical help or contact a Poison Control Center right away.

DIRECTIONS

For sunscreen use:

- Apply liberally 15 minutes before sun exposure.
- Use a water resistant sunscreen if swimming or sweating.
- Reapply at least every 2 hours.
- Children under 6 months: Ask a doctor.
- Sun Protection Measures. Spending time in the sun increases your risk of skin cancer and early skin aging. To decrease this risk, regularly use a sunscreen with a Broad Spectrum SPF value of 15 or higher and other sun protection measures including:
  - Limit time in sun, especially from 10 a.m.-2 p.m.
  - Wear long-sleeved shirts, pants, hats, and sunglasses.

INACTIVE INGREDIENTS

MICA, ZINC STEARATE, SILICA, LAUROYL LYSINE, SQUALANE, ETHYLHEXYL PALMITATE, OCTYLDODECYL STEAROYL STEARATE, ARGANIA SPINOSA KERNEL OIL, GLYCERYL CAPRYLATE, P-ANISIC ACID, TAPIOCA STARCH, POLYMETHYLSILSESQUIOXANE, DIAMOND POWDER, LONICERA CAPRIFOLIUM (HONEYSUCKLE) FLOWER EXTRACT, LONICERA JAPONICA (HONEYSUCKLE) FLOWER EXTRACT, SIMMONDSIA CHINENSIS (JOJOBA) SEED OIL, TOCOPHEROL, RETINYL PALMITATE, HYALURONIC ACID, MYRCIARIA DUBIA FRUIT EXTRACT, CARTHAMUS TINCTORIUS (SAFFLOWER) SEED OIL, PRUNUS AVIUM (SWEET CHERRY) FRUIT EXTRACT, CUMINUM CYMINUM (CUMIN) SEED EXTRACT, ARNICA MONTANA FLOWER EXTRACT, LYCIUM BARBARUM FRUIT EXTRACT MAY CONTAIN: TITANIUM DIOXIDE (CI 77891),IRON OXIDES (CL 77491, CL 77492, CL 77499), BISMUTH OXYCHLORIDE (CI 77163).

OTHER INFORMATION

- Protect this product from excessive heat and direct sun.

QUESTIONS OR COMMENTS

Call toll free 1-800-698-6858

Dist. by Scott-Vincent Borba
Inc. Hollywood, CA 90068.

PRINCIPAL DISPLAY PANEL - 5.6 g Package Carton

SCOTT-VINCENT BORBA

Anti-Fatigue 8 Hour Mineral Foundation
Anti-Wrinkle Treatment Duo
with Broad Spectrum SPF 29

NET WT 0.20 OZ (5.6 g)